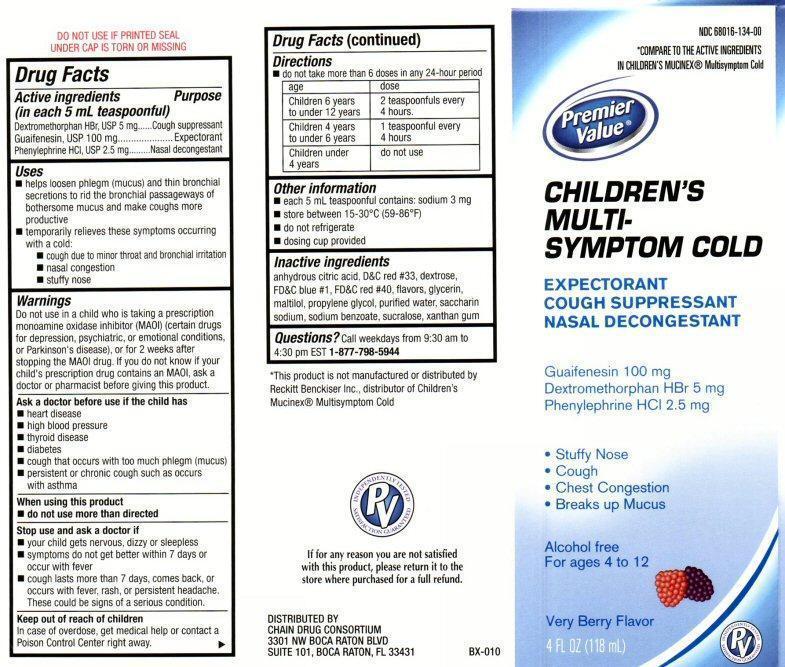 DRUG LABEL: Childrens Multi-Symptom Cold
NDC: 68016-134 | Form: LIQUID
Manufacturer: Chain Drug Consortium, LLC
Category: otc | Type: HUMAN OTC DRUG LABEL
Date: 20130228

ACTIVE INGREDIENTS: GUAIFENESIN 100 mg/5 mL; DEXTROMETHORPHAN HYDROBROMIDE 5 mg/5 mL; PHENYLEPHRINE HYDROCHLORIDE 2.5 mg/5 mL
INACTIVE INGREDIENTS: ANHYDROUS CITRIC ACID; D&C RED NO. 33; DEXTROSE ; FD&C BLUE NO. 1; FD&C RED NO. 40; GLYCERIN; MALTITOL; PROPYLENE GLYCOL; WATER; SACCHARIN SODIUM; SODIUM BENZOATE; SUCRALOSE; XANTHAN GUM

Active ingredients

Drug Facts

Active ingredients

(in each 5 mL teaspoon)

Guaifenesin 100 mg
Dextromethorphan HBr 5 mg
Phenylephrine HCL 2.5 mg

Purpose

Cough suppressant
Expectorant
Nasal decongestant

Keep out of reach of children

In case of overdose, get medical help or contact a Poison Control center right away.

Uses

- helps to loosen phlegm (mucus) and thin bronchial secretions to rid the bronchial passage ways of bothersome mucus and make coughs more productive

- temporarily relieves these symptoms occurring with a cold:

- cough due to minor throat and bronchial irritation

- nasal congestion

- stuffy nose

Warnings

Do not use in a child who is taking a prescription monoamine oxidase inhibitor (MAOI) (certain drugs for depression, psychiatric or emotional conditions, or Parkinson’s disease), or for two weeks after stopping the MAOI drug. If you do not know if your child’s prescription drug contains an MAOI, ask a doctor or a pharmacist before taking this product.

Ask a doctor before use if the child has

- heart disease

- high blood pressure

- thyroid disease

- diabetes

- cough that occurs with too much phlegm (mucus)

- persistent or chronic cough such as occurs with asthma

When using this product

- do not use more than directed

Stop use and ask a doctor if

- your child gets nervous, dizzy, or sleepless

- symptoms do not get better within 7 days or occur with fever

- cough lasts more than 7 days, comes back, or occurs with fever, rash, or persistent headache.

These could be signs of a serious condition.

Directions

- do not take more than 6 doses in any 24-hour period

Age Dose
Children 6 years to under 12 years 2 teaspoons every 4 hours
Children 4 years to under 6 years 1 teaspoon every 4 hours
Children under 4 years Do not use

Other information

- each 5 mL teaspoon contains: sodium 3 mg

- store between 15-30 ° C (59-86° F)

- do not refrigerate

- dosing cup provided

Inactive ingredients

citric acid anhydrous, D and C red #33,dextrose, FD and C blue #1, FD and C red # 40, flavors, glycerin, maltitol, propylene glycol, purified water, saccharin sodium, sodium benzoate, sucralose, xanthan gum

Questions?

Call weekdays from 9:30 AM to 4:30 PM EST at

1-877-798-5944

Product Label

NDC 68016-134-00

*COMPARE TO THE ACTIVE INGREDIENTS IN CHILDREN’S MUCINEX®Multisymptom Cold

Premier Value®
CHILDREN’S MULTI- SYMPTOM COLD

EXPECTORANT
COUGH SUPPRESSANT
NASAL DECONGESTANT

Guaifenesin 100 mg
Dextromethorphan HBr 5 mg
Phenylephrine HCL 2.5 mg

* Stuffy Nose
* Cough
* Chest Congestion
* Breaks up Mucus

Alcohol free

For ages 4 to 12

Very Berry Flavor
4 FL OZ (118mL)

INDEPENDENTLY TESTED SATISFACTION GUARANTEED PV
DO NOT USE IF PRINTED SEAL UNDER CAP IS TORN OR MISSING

*This product is not manufactured or distributed by Reckitt Benckiser Inc. distributor of Children’s Mucinex® Multisymptom Cold
If for Any reason you are not satisfied with this product, lease return it to the store where purchased for a full refund.
DISTRIBUTED BY
CHAIN DRUG CONSORTIUM
3301 NW BOCA RATON BLVD
SUITE 101, BOCA RATON, FL 33431
BX-010